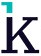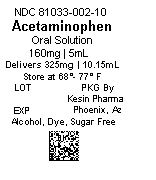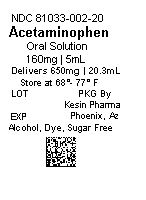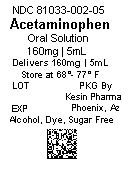 DRUG LABEL: Acetaminophen
NDC: 81033-002 | Form: SOLUTION
Manufacturer: Kesin Pharma Corporation
Category: otc | Type: HUMAN OTC DRUG LABEL
Date: 20241203

ACTIVE INGREDIENTS: ACETAMINOPHEN 160 mg/5 mL
INACTIVE INGREDIENTS: ANHYDROUS CITRIC ACID; METHYLPARABEN; PROPYLPARABEN; PROPYLENE GLYCOL; SORBITOL; AMMONIUM GLYCYRRHIZATE; POTASSIUM CITRATE; WATER; SUCRALOSE

5mL, 10.15mL, 20.3mL, ACETAMINOPHEN oral solution 160mg per 5mL, 10.15mL

ACETAMINOPHEN Oral Solution 160mg per 5mL

ACETAMINOPHEN Oral Solution
160mg per 5mL

Active Ingredients (in each 5 mL)

Acetaminophen 160 mg

PURPOSE

Pain reliever/fever reducer

USES

Temporarily relieves minor aches and pains due to:

- headaches
- backaches
- toothaches
- muscular aches
- minor pain of arthritis
- the common cold
- premenstrual and menstrual cramps
- sore throat
- flu

Temporarily reduces fever

WARNINGS

Liver warning: This product contains acetaminophen. Severe liver damage may occur if:

- adult takes more than more than 6 doses in in 24 hours, which is the maximum daily amount
- child takes more than 5 doses in 24 hours
- taken with other drugs containing acetaminophen
- adult has 3 or more alcoholic drinks everyday while using this product

Ask a doctor before use if the user has liver disease.
Allergy alert: Acetaminophen may cause severe skin reactions.

Symptoms may include:

- skin reddening
- blisters
- rash

If a skin reaction occurs, stop use and seek medical help right away.

Sore throat warning: If sore throat is severe, persistent for more than 2 days, or is accompanied or followed by a fever,
headache, nausea, rash, or vomiting, consult a physician promptly.

Do not use

- with any other drug containing acetaminophen (prescription or nonprescription). If you are not sure whether a drug contains acetaminophen, ask a doctor or pharmacist.

- for more than 3 days for fever unless directed by a doctor

- for more that 10 days for pain unless directed by a doctor

- if you are allergic to acetaminophen or any of the inactive ingredients in this product

Ask a doctor or pharmacist before use if the user is taking the blood thinning drug warfarin.

Stop use and ask a doctor if

- symptoms do not improve
- new symptoms occur
- pain gets worse or lasts more than 5 days
- fever gets worse or lasts more than 3 days
- redness or swelling is present

These could be signs of a serious condition.

If Pregnant or breast-feedinging

If pregnant or breast-feeding, ask a health professional before use.

Keep out of reach of children.

Overdose warning:

Overdose warning: Taking more than the recommended dose (overdose) may cause liver damage. In case of overdose, get
medical help or contact a Poison Control Center right away (1-800-222-1222). Quick medical attention is critical for adults as
well as for children even if you do not notice any signs or symptoms.

DIRECTIONS

- do not take more than directed (see overdose warning)

Age | Dose
adults and children 12 years of age and over | 20.3 mL (650 mg) every 4 to 6 hours not to excdeed 6 doses in a 24-hour period
children 6 to Under 12 years of age | 10.15 mL (325 mg) every 4 hours not to exceed 5 doses in a 24-hour period
children 4 to under 6 years of age | 7.5 mL (240 mg) every 4 hours not to exceed 5 doses in a 24-hour period
children under 2 years of age | consult a doctor

OTHER INFORMATION

- store at 20° to 25°C (68° to 77°F). [See USP Controlled Room Temperature].
- keep tightly closed
- protect from light
- tamper evident: DO NOT use if foil on cup is missing or torn
- a clear, grape flavored solution supplied in the following oral dosage forms:

NDC 81033-002-05: 5 mL (160mg) unit dose cup
NDC 81033-002-55: Case contains 100 unit dose cups of 5 mL (81033-002-05); packaged in a carton of 50 unit dose cups each.
NDC 81033-002-10: 10.15mL (325mg) unit dose cup
NDC 81033-002-54: Case contains 100 unit dose cups of 10.15 mL (81033-002-10); packaged in a carton of 50 unit dose cups
each.
NDC 81033-002-20: 20.3 mL (650mg) unit dose cup
NDC 81033-002-53: Case contains 100 unit dose cups of 20.3 mL (81033-002-20); packaged in a carton of 50 unit dose cups
each.

INACTIVE INGREDIENTS

Citric acid, grape flavor, methylparaben, monoammonium glycyrrhizinate, potassium citrate, propylene glycol, propylparaben, purified water, sorbitol, sucralose

QUESTIONS OR COMMENTS?

Call Kesin Pharma at 1-833-537-4679. You may also report serious side effects to this phone number.

Packaged by:
Kesin Pharma
Oldsmar, FL 34677
Effective: 08/2024

Revision 01

PRINCIPAL DISPLAY PANEL

NDC 81033-002-05

Acetaminophen Oral Solution

160mg/5mL

Delivers160mg/5mL

Store at 68° - 77° F

LOT

EXP

PKG by Kesin Pharma

Oldsmar, FL

Alcohol, Dye, Sugar Free

For Institutional Use

NDC 81033-002-10

Acetaminophen Oral Solution

160mg/5mL

Delivers 325mg/10.15mL

Store at 68° - 77° F

LOT

EXP

PKG by Kesin Pharma

Oldsmar, FL

Alcohol, Dye, Sugar Free

For Institutional Use

NDC 81033-002-20

Acetaminophen Oral Solution

160mg/5mL

Delivers 650mg/20.15mL

Store at 68° - 77° F

LOT

EXP

PKG by Kesin Pharma

Oldsmar, FL

Alcohol, Dye, Sugar Free

For Institutional Use